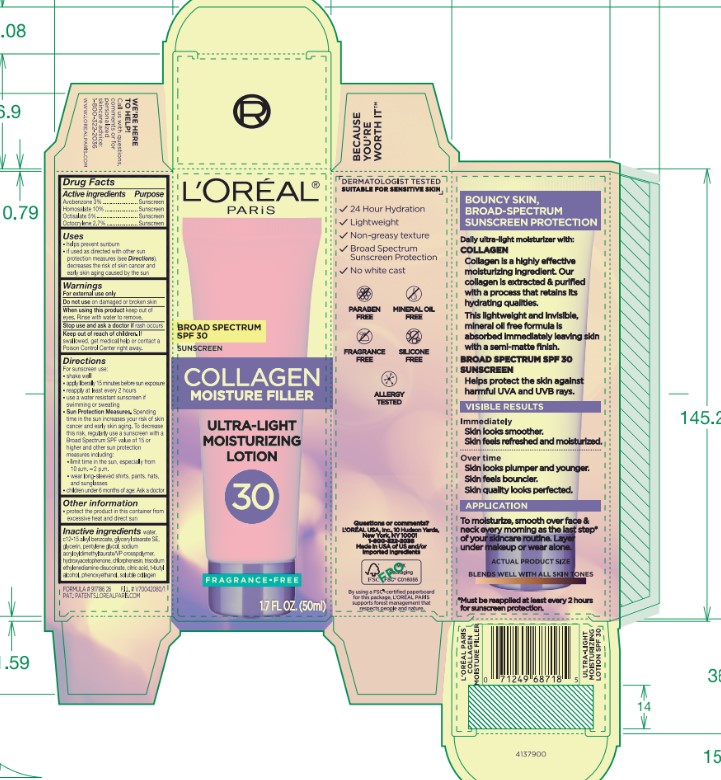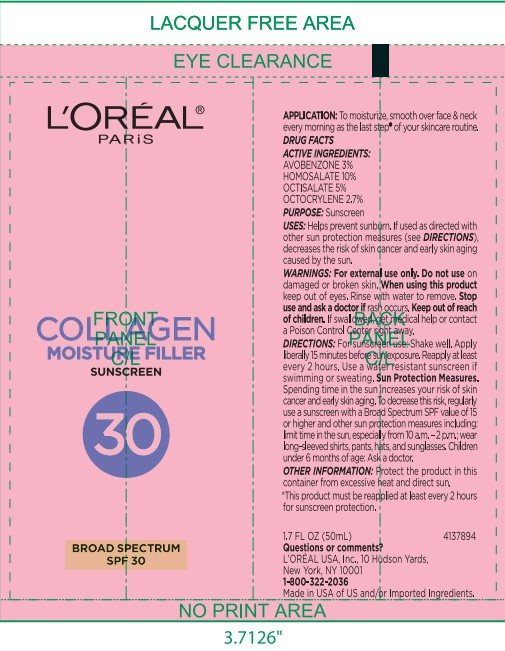 DRUG LABEL: LOreal Paris Collagen Moisture Filler Ultra Light Moisturizing Broad Spectrum SPF 30 Sunscreen
NDC: 49967-718 | Form: LOTION
Manufacturer: L'Oreal USA Products Inc
Category: otc | Type: HUMAN OTC DRUG LABEL
Date: 20240628

ACTIVE INGREDIENTS: Avobenzone 30 mg/1 mL; Homosalate 100 mg/1 mL; Octisalate 50 mg/1 mL; Octocrylene 27 mg/1 mL
INACTIVE INGREDIENTS: WATER; ALKYL (C12-15) BENZOATE; GLYCERYL STEARATE SE; GLYCERIN; PENTYLENE GLYCOL; HYDROXYACETOPHENONE; CHLORPHENESIN; TRISODIUM ETHYLENEDIAMINE DISUCCINATE; CITRIC ACID MONOHYDRATE; TERT-BUTYL ALCOHOL; PHENOXYETHANOL

Drug Facts

Active ingredients

Avobenzone 3%

Homosalate 10%

Octisalate 5%

Octocrylene 2.7%

Purpose

Sunscreen

Uses

- helps prevent sunburn
- if used as directed with other sun protection measures (see Directions), decreases the risk of skin cancer and early skin aging caused by the sun

Warnings

For external use only

Do not use

on damaged or broken skin

When using this product

keep out of eyes. Rinse with water to remove.

Stop use and ask a doctor if

rash occurs

Keep out of reach of children.

If swallowed, get medical help or contact a Poison Control Center right away.

Directions

For sunscreen use:

- shake well
- apply liberally 15 minutes before sun exposure
- reapply at least every 2 hours
- use a water resistant sunscren if swimming or sweating
- Sun Protection Measures. Spending time in the sun increases your risk of skin cancer and early skin aging. To decrease this risk, regularly use a sunscreen with a Broad Spectrum SPF value of 15 or higher and other sun protection measures including:
- limit time in the sun, especially from 10 a.m. - 2 p.m.
- wear long-sleeved shirts, pants, hats, and sunglasses
- children under 6 months of age: Ask a doctor

Other information

- protect the product in this container from excessive heat and direct sun

Inactive ingredients

water, c12-15 alkyl benzoate, glyceryl stearate SE, glycerin, pentylene glycol, sodium acryloyldimethyltaurate/VP crosspolymer, hydroxyacetophenone, chlorphenesin, trisodium ethylenediamine disuccinate, citric acid, t-butyl alcohol, phenoxyethanol, soluble collagen

Questions or comments?

L'OREAL USA, Inc., 10 Hudson Yards,

New York, NY 10001

1-800-322-2046

Made in USA of US and/or Imported Ingredients